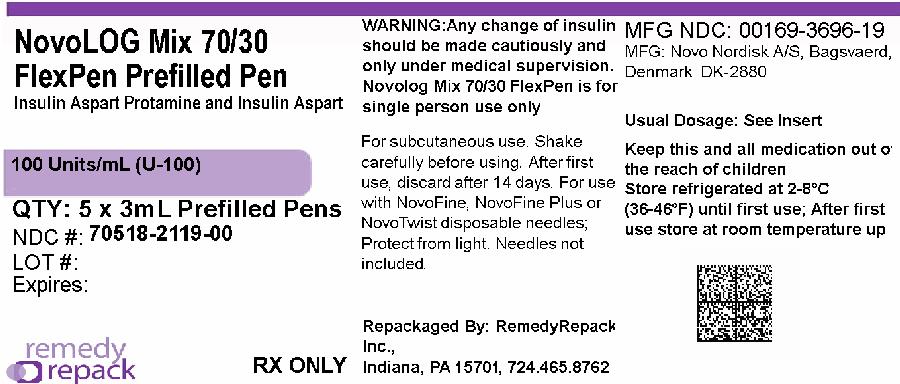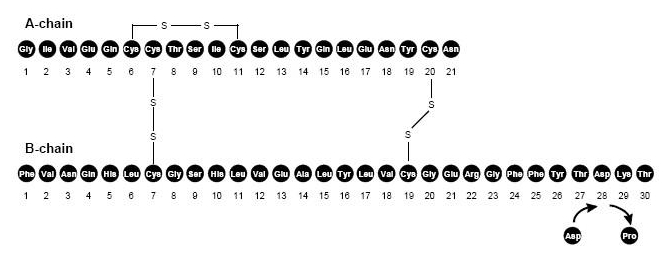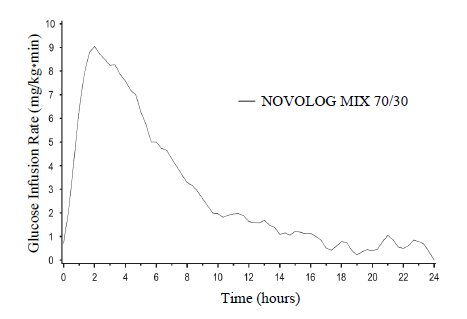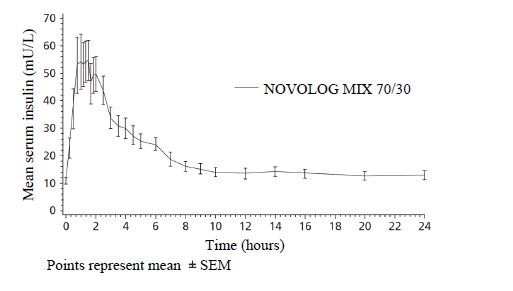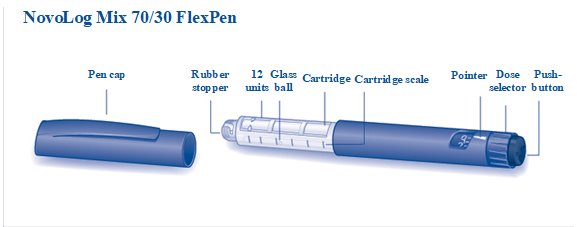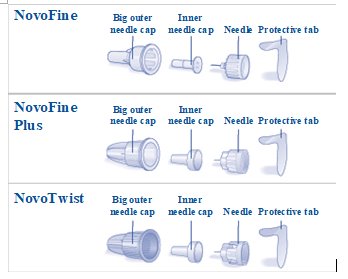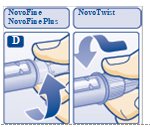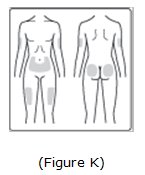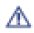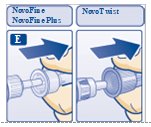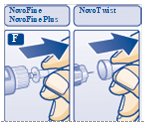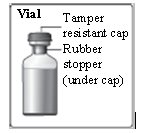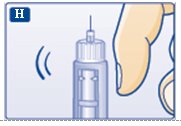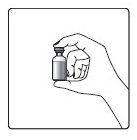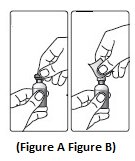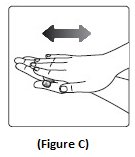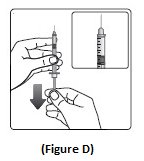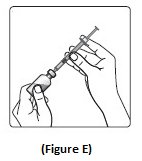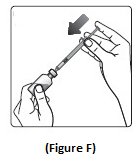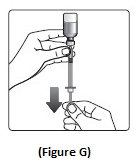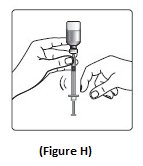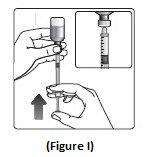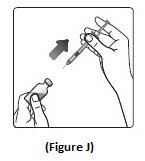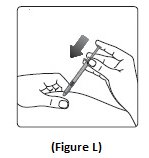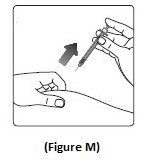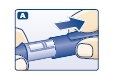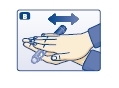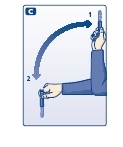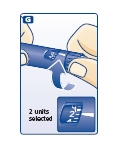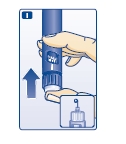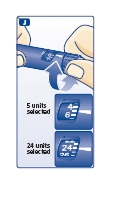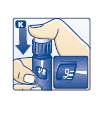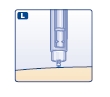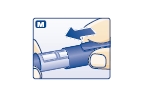 DRUG LABEL: NovoLog Mix 70/30
NDC: 70518-2119 | Form: INJECTION, SUSPENSION
Manufacturer: REMEDYREPACK INC.
Category: prescription | Type: HUMAN PRESCRIPTION DRUG LABEL
Date: 20260130

ACTIVE INGREDIENTS: INSULIN ASPART 100 [iU]/1 mL
INACTIVE INGREDIENTS: GLYCERIN 16 mg/1 mL; HYDROCHLORIC ACID; METACRESOL 1.72 mg/1 mL; PHENOL 1.5 mg/1 mL; PROTAMINE SULFATE 0.32 mg/1 mL; SODIUM CHLORIDE 0.877 mg/1 mL; SODIUM HYDROXIDE; ZINC 19.6 ug/1 mL; SODIUM PHOSPHATE, DIBASIC, DIHYDRATE 1.25 mg/1 mL

HIGHLIGHTS OF PRESCRIBING INFORMATION

These highlights do not include all the information needed to use NOVOLOG MIX 70/30 safely and effectively. See full prescribing information for NOVOLOG MIX 70/30.
NOVOLOG®MIX 70/30 (insulin aspart protamine and insulin aspart) injectable suspension, for subcutaneous use
Initial U.S. Approval: 2001

1 INDICATIONS AND USAGE

NOVOLOG MIX 70/30 is a mixture of insulin aspart protamine, an intermediate-acting human insulin analog, and insulin aspart, a rapid-acting human insulin analog, indicated to improve glycemic control in adult patients with diabetes mellitus.

Limitations of Use:

- Not recommended for the treatment of diabetic ketoacidosis.
- The proportions of rapid-acting and long-acting insulins are fixed and do not allow for basal versus prandial dose adjustments (1).

2 DOSAGE AND ADMINISTRATION

- Inspect visually before use. Appearance should be uniformly white and cloudy. Do not use it if it looks clear or if it contains solid particles (2.1).
- NOVOLOG MIX 70/30 must be resuspended immediately before use. Resuspension is easier when the insulin has reached room temperature (2.1).
- Inject NOVOLOG MIX 70/30 subcutaneously in the abdominal region, buttocks, thigh, or upper arm (2.1).
- Administer the dose within 15 minutes before meal initiation. For patients with type 2 diabetes, the dose may also be given after meal initiation (2.1).
- Rotate injection sites within the same region from one injection to the next to reduce risk of lipodystrophy and localized cutaneous amyloidosis (2.1).
- Do notadminister intravenously or use in insulin infusion pumps (2.1).
- NOVOLOG MIX 70/30 is typically dosed twice-daily (with each dose intended to cover 2 meals or a meal and a snack) (2.2).
- Individualize dosage based on metabolic needs, blood glucose monitoring results, glycemic control goal (2.2).
- Dosage adjustments may be needed with changes in physical activity, changes in meal patterns (i.e., macronutrient content or timing of food intake), changes in renal or hepatic function or during acute illness (2.2).
- When switching from another insulin to NOVOLOG MIX 70/30, a different dosage of NOVOLOG MIX 70/30 may be needed (2.2).

3 DOSAGE FORMS AND STRENGTHS

Injectable suspension: 100 units/mL (U-100) of NOVOLOG MIX 70/30, 70% insulin aspart protamine and 30% insulin aspart available as:

- 3 mL single-patient-use FlexPen prefilled pen (3)

4 CONTRAINDICATIONS

- Do not use during episodes of hypoglycemia (4).
- Do not use in patients with hypersensitivity to NOVOLOG MIX 70/30 or one of its excipients (4).

5 WARNINGS AND PRECAUTIONS

- Never share a NOVOLOG MIX 70/30 FlexPen between patients, even if the needle is changed (5.1).
- Hyperglycemia or hypoglycemia with changes in insulin regimen:Make changes to a patient’s insulin regimen (e.g., insulin strength, manufacturer, type, injection site or method of administration) under close medical supervision with increased frequency of blood glucose monitoring (5.2).
- Hypoglycemia:May be life-threatening. Increase frequency of glucose monitoring with changes to: insulin dosage, concomitantly administered glucose lowering medications, meal pattern, physical activity; and in patients with renal or hepatic impairments and hypoglycemia unawareness (5.3).
- Medication Errors:Accidental mix-ups between insulin products can occur. Instruct patients to check insulin labels before injection (5.4).
- Hypersensitivity reactions:Severe, life-threatening, generalized allergy, including anaphylaxis, may occur. Discontinue NOVOLOG MIX 70/30, treat, and monitor, if indicated (5.5).
- Hypokalemia:May be life-threatening. Monitor potassium levels in patients at risk of hypokalemia and treat if indicated (5.6).
- Fluid retention and heart failure withconcomitant use of thiazolidinediones (TZDs): Observe for signs and symptoms of heart failure; consider dosage reduction or discontinuation if heart failure occurs (5.7).

6 ADVERSE REACTIONS

Adverse reactions observed with insulin therapy include hypoglycemia, allergic reactions, local injection site reactions, lipodystrophy, rash and pruritus (6).

- To report SUSPECTED ADVERSE REACTIONS, contact Novo Nordisk Inc. at 1-800-727-6500 or FDA at 1-800-FDA-1088 or www.fda.gov/medwatch.

7 DRUG INTERACTIONS

- Drugs that may increase the risk of hypoglycemia:antidiabetic agents, ACE inhibitors, angiotensin II receptor blocking agents, disopyramide, fibrates, fluoxetine, monoamine oxidase inhibitors, pentoxifylline, pramlintide, salicylates, somatostatin analog (e.g., octreotide), and sulfonamide antibiotics (7).
- Drugs that may decrease the blood glucose lowering effect:atypical antipsychotics, corticosteroids, danazol, diuretics, estrogens, glucagon, isoniazid, niacin, oral contraceptives, phenothiazines, progestogens (e.g., in oral contraceptives), protease inhibitors, somatropin, sympathomimetic agents (e.g., albuterol, epinephrine, terbutaline), and thyroid hormones (7).
- Drugs that may increase or decrease the blood glucose lowering effect:alcohol, beta-blockers, clonidine, lithium salts, and pentamidine (7).
- Drugs that may bluntthe signs and symptoms of hypoglycemia:beta-blockers, clonidine, guanethidine, and reserpine (7).

FULL PRESCRIBING INFORMATION

1 INDICATIONS AND USAGE

NOVOLOG MIX 70/30 is a mixture of insulin aspart protamine and insulin aspart indicated to improve glycemic control in adult patients with diabetes mellitus.

Limitations of Use:

- NOVOLOG MIX 70/30 is not recommended for the treatment of diabetic ketoacidosis.
- The proportions of rapid-acting and long-acting insulins in NOVOLOG MIX 70/30 are fixed and do not allow for basal versus prandial dose adjustments.

2 DOSAGE AND ADMINISTRATION

2.1 Important Preparation and Administration Instructions

- Always check insulin labels before administration [see Warnings and Precautions (5.4)].
- Inspect NOVOLOG MIX 70/30 visually before use. It should appear uniformly white and cloudy. Do not use it if it looks clear or if it contains solid particles.
- NOVOLOG MIX 70/30 must be resuspended immediately before use. Resuspension is easier when the insulin has reached room temperature.
- When using the:
- Vial, roll the vial gently in hands in a horizontal position 10 times until the suspension appears uniformly white and cloudy. Inject immediately.
- NOVOLOG MIX 70/30 FlexPen, roll NOVOLOG MIX 70/30 FlexPen gently between hands in a horizontal position 10 times. Then, turn NOVOLOG MIX 70/30 FlexPen upside down so that the glass ball moves from one end of the reservoir to the other 10 times until the suspension appears uniformly white and cloudy. Inject immediately.
- The NOVOLOG MIX 70/30 FlexPen dials in 1-unit increments.
- Use NOVOLOG MIX 70/30 FlexPen with caution in patients with visual impairment who may rely on audible clicks to dial their dose.
- Inject NOVOLOG MIX 70/30 subcutaneously in the abdominal region, buttocks, thigh, or upper arm.
- Administer the dose within 15 minutes before meal initiation. For patients with type 2 diabetes, the dose may also be given after meal initiation.
- Rotate injection sites within the same region from one injection to the next to reduce the risk of lipodystrophy and localized cutaneous amyloidosis. Do not inject into areas of lipodystrophy or localized cutaneous amyloidosis [see Warnings and Precautions (5.2)and Adverse Reactions(6.1, 6.3)].
- Do notadminister NOVOLOG MIX 70/30 intravenously or use in insulin infusion pumps.
- Do notmix NOVOLOG MIX 70/30 with any other insulins.

2.2 Dosage Recommendations

- NOVOLOG MIX 70/30 is typically dosed twice-daily (with each dose intended to cover 2 meals or a meal and a snack).
- Individualize the dosage of NOVOLOG MIX 70/30 based on the patient's metabolic needs, blood glucose monitoring results and glycemic control goal.
- Dosage adjustments may be needed with changes in physical activity, changes in meal patterns (i.e., macronutrient content or timing of food intake), changes in renal or hepatic function or during acute illness [see Warnings and Precautions (5.3) and Use in Specific Populations (8.6, 8.7)] .
- When switching from another insulin to NOVOLOG MIX 70/30, a different dosage of NOVOLOG MIX 70/30 may be needed [see Warnings and Precautions (5.2)].
- During changes to a patient’s insulin regimen, increase the frequency of blood glucose monitoring [see Warnings and Precautions (5.2)].

2.3 Dosage Modifications for Drug Interactions

Dosage modification may be needed when NOVOLOG MIX 70/30 is used concomitantly with certain drugs [see Drug Interactions (7)].

3 DOSAGE FORMS AND STRENGTHS

Injectable suspension: 100 units/mL (U-100) of NOVOLOG MIX 70/30, 70% insulin aspart protamine and 30% insulin aspart, is a white and cloudy suspension available as:

- 3 mL single-patient-use FlexPen prefilled pen

4 CONTRAINDICATIONS

NOVOLOG MIX 70/30 is contraindicated:

- During episodes of hypoglycemia [ see Warnings and Precautions (5.3)]
- In patients with hypersensitivity to NOVOLOG MIX 70/30 or one of its excipients [see Warnings and Precautions (5.5)]

5 WARNINGS AND PRECAUTIONS

5.1 Never Share NOVOLOG MIX 70/30 FlexPen Between Patients

NOVOLOG MIX 70/30 FlexPen should never be shared between patients, even if the needle is changed. Patients using NOVOLOG MIX 70/30 vials must never share needles or syringes with another person. Sharing poses a risk for transmission of blood-borne pathogens.

5.2 Hyperglycemia or Hypoglycemia with Changes in Insulin Regimen

Changes in an insulin regimen (e.g., insulin strength, manufacturer, type, injection site or method of administration) may affect glycemic control and predispose to hypoglycemia [ see Warnings and Precautions (5.3)] or hyperglycemia. Repeated insulin injections into areas of lipodystrophy or localized cutaneous amyloidosis have been reported to result in hyperglycemia; and a sudden change in the injection site (to an unaffected area) has been reported to result in hypoglycemia [ see Adverse Reactions(6.1, 6.3)] . Make any changes to a patient’s insulin regimen under close medical supervision with increased frequency of blood glucose monitoring. Advise patients who have repeatedly injected into areas of lipodystrophy or localized cutaneous amyloidosis to change the injection site to unaffected areas and closely monitor for hypoglycemia. For patients with type 2 diabetes, dosage adjustments of concomitant anti-diabetic products may be needed.

5.3 Hypoglycemia

Hypoglycemia is the most common adverse reaction of all insulins, including NOVOLOG MIX 70/30. Severe hypoglycemia can cause seizures, may lead to unconsciousness, may be life threatening or cause death. Hypoglycemia can impair concentration ability and reaction time; this may place an individual and others at risk in situations where these abilities are important (e.g., driving or operating other machinery).

Hypoglycemia can happen suddenly and symptoms may differ in each individual and change over time in the same individual. Symptomatic awareness of hypoglycemia may be less pronounced in patients with longstanding diabetes in patients with diabetic nerve disease, in patients using medications that block the sympathetic nervous system (e.g., beta-blockers) [see Drug Interactions (7)], or in patients who experience recurrent hypoglycemia.

Risk Factors for Hypoglycemia

The risk of hypoglycemia after an injection is related to the duration of action of the insulin and, in general, is highest when the glucose lowering effect of the insulin is maximal. As with all insulins, the glucose lowering effect time course of NOVOLOG MIX 70/30 may vary in different individuals or at different times in the same individual and depends on many conditions, including the area of injection as well as the injection site blood supply and temperature [see Clinical Pharmacology (12.2)]. Other factors which may increase the risk of hypoglycemia include changes in meal pattern (e.g., macronutrient content or timing of meals), changes in level of physical activity, or changes to concomitantly administered medication [see Drug Interactions (7)]. Patients with renal or hepatic impairment may be at higher risk of hypoglycemia [see Use in Specific Populations (8.6, 8.7)].

Risk Mitigation Strategies for Hypoglycemia

Patients and caregivers must be educated to recognize and manage hypoglycemia. Self-monitoring of blood glucose plays an essential role in the prevention and management of hypoglycemia; increased frequency of blood glucose monitoring is recommended. In patients at higher risk for hypoglycemia and patients who have reduced symptomatic awareness of hypoglycemia, increased frequency of blood glucose monitoring is recommended.

5.4 Hypoglycemia Due to Medication Errors

Accidental mix-ups between insulin products have been reported. To avoid medication errors between NOVOLOG MIX 70/30 and other insulins, instruct patients to always check the insulin label before each injection.

5.5 Hypersensitivity Reactions

Severe, life-threatening, generalized allergy, including anaphylaxis, can occur with insulins, including NOVOLOG MIX 70/30. If hypersensitivity reactions occur, discontinue NOVOLOG MIX 70/30; treat per standard of care and monitor until symptoms and signs resolve [see Adverse Reactions (6)]. NOVOLOG MIX 70/30 is contraindicated in patients who have had hypersensitivity reactions to insulin aspart or one of the excipients [see Contraindications (4)].

5.6 Hypokalemia

All insulins, including NOVOLOG MIX 70/30, can cause a shift in potassium from the extracellular to intracellular space, possibly leading to hypokalemia. Untreated hypokalemia may cause respiratory paralysis, ventricular arrhythmia, and death. Monitor potassium levels in patients at risk for hypokalemia if indicated (e.g., patients using potassium-lowering medications, patients taking medications sensitive to serum potassium concentration).

5.7 Fluid Retention and Heart Failure with Concomitant Use of PPAR-gamma Agonists

Thiazolidinediones (TZDs), which are peroxisome proliferator-activated receptor (PPAR)-gamma agonists, can cause dose-related fluid retention, particularly when used in combination with insulin. Fluid retention may lead to or exacerbate heart failure. Patients treated with insulin, including NOVOLOG MIX 70/30, and a PPAR-gamma agonist should be observed for signs and symptoms of heart failure. If heart failure develops, it should be managed according to current standards of care, and discontinuation or dose reduction of the PPAR-gamma agonist must be considered.

6 ADVERSE REACTIONS

The following adverse reactions are also discussed elsewhere:

- Hypoglycemia [ see Warnings and Precautions (5.3)]
- Hypoglycemia Due to Medication Errors [ see Warnings and Precautions (5.4)]
- Hypersensitivity reactions [ see Warnings and Precautions (5.5)]
- Hypokalemia [ see Warnings and Precautions (5.6)]

6.1 Clinical Trial Experience

Clinical trials are conducted under widely varying designs, therefore, the adverse reaction rates reported in one clinical trial may not be easily compared to those rates reported in another clinical trial, and may not reflect the rates actually observed in clinical practice. The data in:

- Table 1 reflects the exposure of 55 patients with type 1 diabetes to NOVOLOG MIX 70/30 with a mean exposure duration of three months. The mean age was 43 years old. Sixty-four percent were male and 100% were White. The mean body mass index (BMI) was 26.1 kg/m^2. The mean duration of diabetes was 15 years.
- Table 2 reflects the exposure of 85 patients with type 2 diabetes to NOVOLOG MIX 70/30 with a mean exposure duration of three months. The mean age was 63 years old. Fifty-four percent were male and 100% were White. The mean body mass index (BMI) was 28.1 kg/m^2. The mean duration of diabetes was 15 years.

Common adverse reactions were defined as events that occurred in ≥5%, excluding hypoglycemia, of the population studied. Common adverse reactions that occurred for NOVOLOG MIX 70/30-treated patients with type 1 diabetes mellitus and type 2 diabetes mellitus are listed in Table 1 and Table 2, respectively. The trial was a three-month, open-label trial in patients with type 1 or type 2 diabetes who were treated twice daily (before breakfast and before supper) with NOVOLOG MIX 70/30.

Table 1: Adverse Reactions that Occurred in ≥ 5% of Type 1 Diabetes Mellitus Adult Patients Treated with NOVOLOG MIX 70/30

 | NOVOLOG MIX 70/30; (n=55)
Preferred Term | N | %
Hypoglycemia | 38 | 69
Headache | 19 | 35
Influenza-like symptoms | 7 | 13
Dyspepsia | 5 | 9
Back pain | 4 | 7
Diarrhea | 4 | 7
Pharyngitis | 4 | 7
Rhinitis | 3 | 5
Skeletal pain | 3 | 5
Upper respiratory tract infection | 3 | 5

Table 2: Adverse Reactions that Occurred in ≥ 5% of Type 2 Diabetes Mellitus Adult Patients Treated with NOVOLOG MIX 70/30

 | NOVOLOG MIX 70/30; (n=85)
Preferred Term | N | %
Hypoglycemia | 40 | 47
Upper respiratory tract infection | 10 | 12
Headache | 8 | 9
Diarrhea | 7 | 8
Neuropathy | 7 | 8
Pharyngitis | 5 | 6
Abdominal pain | 4 | 5
Rhinitis | 4 | 5

Severe Hypoglycemia

Hypoglycemia is the most commonly observed adverse reaction in patients using insulin, including NOVOLOG MIX 70/30 .The rates of reported hypoglycemia depend on the definition of hypoglycemia used, diabetes type, insulin dose, intensity of glucose control, background therapies, and other intrinsic and extrinsic patient factors. For these reasons, comparing rates of hypoglycemia in clinical trials for NOVOLOG MIX 70/30 with the incidence of hypoglycemia for other products may be misleading and also, may not be representative of hypoglycemia rates that will occur in clinical practice.

Severe hypoglycemia requiring the assistance of another person and/or parenteral glucose infusion or glucagon administration has been observed in clinical trials with insulin, including trials with NOVOLOG MIX 70/30.

The incidence of severe hypoglycemia in adult patients receiving subcutaneous NOVOLOG MIX 70/30 was 16% and 4% for type 1 and type 2 diabetes patients respectively at 12 weeks [see Clinical Studies (14)].

Allergic Reactions

Patients have experienced reactions such as erythema, edema or pruritus at the site of NOVOLOG MIX 70/30 injection. These reactions usually resolve in a few days to a few weeks, but in some occasions, have required discontinuation of NOVOLOG MIX 70/30. Severe cases of generalized allergy (anaphylaxis) have been reported.

Adverse Reactions Associated with Insulin Initiation and Glucose Control Intensification

Intensification or rapid improvement in glucose control has been associated with transitory, reversible ophthalmologic refraction disorder, worsening of diabetic retinopathy, and acute painful peripheral neuropathy. However, long-term glycemic control decreases the risk of diabetic retinopathy and neuropathy.

Lipodystrophy

Long-term use of insulin, including NOVOLOG MIX 70/30, can cause lipodystrophy at the site of repeated insulin injections. Lipodystrophy includes lipohypertrophy (thickening of adipose tissue) and lipoatrophy (thinning of adipose tissue), and may affect insulin absorption [see Dosage and Administration (2.1)].

Weight Gain

Weight gain can occur with insulins, including NOVOLOG MIX 70/30, and has been attributed to the anabolic effects of insulin and the decrease in glycosuria.

Peripheral Edema

Insulins, including NOVOLOG MIX 70/30, may cause sodium retention and edema, particularly if previously poor metabolic control is improved by intensified insulin therapy.

6.2 Immunogenicity

As with all therapeutic proteins, there is potential for immunogenicity. The detection of antibody formation is highly dependent on the sensitivity and specificity of the assay. Additionally, the observed incidence of antibody (including neutralizing antibody) positivity in an assay may be influenced by several factors including assay methodology, sample handling, timing of sample collection, concomitant medications, and underlying disease. For these reasons, comparison of the incidence of antibodies to NOVOLOG MIX 70/30 in the studies described below with the incidence of antibodies in other studies or to other products may be misleading.

In a 3-month study with an extension in adult patients with type 2 diabetes, 100% of patients who received NOVOLOG MIX 70/30 were positive for anti-insulin antibodies (AIA) at least once during the first 12 months of the study including 91.4% that were positive at baseline. A total of 91.4% of patients who received NOVOLOG MIX 70/30 were positive for anti-drug antibodies (ADA) at least once during the first 12 months of the study, including 62.1% that were positive at baseline.

In a type 2 diabetes clinical trial of NOVOLOG MIX 70/30, initial increase in titers of antibodies to insulin followed by a decrease approaching to baseline values was observed in NOVOLOG MIX 70/30 and Novolin 70/30 treatment groups with similar incidences. These antibodies did not cause deterioration in glycemic control or necessitate increases in insulin dose.

6.3 Postmarketing Experience

The following adverse reactions have been identified during post-approval use of NOVOLOG MIX 70/30. Because these adverse reactions are reported voluntarily from a population of uncertain size, it is generally not possible to reliably estimate their frequency or establish a causal relationship to drug exposure.

Medication errors in which other insulins have been accidentally substituted for NOVOLOG MIX 70/30 have been reported.

Localized cutaneous amyloidosis at the injection site has occurred with insulin aspart. Hyperglycemia has been reported with repeated insulin injections into areas of localized cutaneous amyloidosis; hypoglycemia has been reported with a sudden change to an unaffected injection site.

7 DRUG INTERACTIONS

The table below presents clinically significant drug interactions with NOVOLOG MIX 70/30.

Table 3: Clinically Significant Drug Interactions with NOVOLOG MIX 70/30

Drugs that May Increase the Risk of Hypoglycemia
Drugs: | Antidiabetic agents, ACE inhibitors, angiotensin II receptor blocking agents, disopyramide, fibrates, fluoxetine, monoamine oxidase inhibitors, pentoxifylline, pramlintide, salicylates, somatostatin analog (e.g., octreotide), and sulfonamide antibiotics
Intervention: | Dose adjustment and increased frequency of glucose monitoring may be required when NOVOLOG MIX 70/30 is concomitantly administered with these drugs.
Drugs that May Decrease the Blood Glucose Lowering Effect of NOVOLOG MIX 70/30
Drugs: | Atypical antipsychotics (e.g., olanzapine and clozapine), corticosteroids, danazol, diuretics, estrogens, glucagon, isoniazid, niacin, oral contraceptives, phenothiazines, progestogens (e.g., in oral contraceptives), protease inhibitors, somatropin, sympathomimetic agents (e.g., albuterol, epinephrine, terbutaline), and thyroid hormones.
Intervention: | Dose adjustment and increased frequency of glucose monitoring may be required when NOVOLOG MIX 70/30 is concomitantly administered with these drugs.
Drugs that May Increase or Decrease the Blood Glucose Lowering Effect of NOVOLOG MIX 70/30
Drugs: | Alcohol, beta-blockers, clonidine, and lithium salts. Pentamidine may cause hypoglycemia, which may sometimes be followed by hyperglycemia.
Intervention: | Dose adjustment and increased frequency of glucose monitoring may be required when NOVOLOG MIX 70/30 is concomitantly administered with these drugs.
Drugs that May Blunt Signs and Symptoms of Hypoglycemia
Drugs: | Beta-blockers, clonidine, guanethidine, and reserpine
Intervention: | Increased frequency of glucose monitoring may be required when NOVOLOG MIX 70/30 is concomitantly administered with these drugs.

8 USE IN SPECIFIC POPULATIONS

8.1 Pregnancy

Risk Summary

There are no available data with NOVOLOG MIX 70/30 in pregnant women to inform a drug-associated risk for major birth defects and miscarriage. Available information from published randomized controlled trials with insulin aspart use during the second trimester of pregnancy have not reported an association with insulin aspart and major birth defects or adverse maternal or fetal outcomes [see Data]. There are risks to the mother and fetus associated with poorly controlled diabetes in pregnancy [see Clinical Considerations].

In animal reproduction studies, administration of subcutaneous insulin aspart to pregnant rats and rabbits during the period of organogenesis did not cause adverse developmental effects at exposures 8-times and equal to the human subcutaneous dose of 1 unit/kg/day, respectively. Pre- and post-implantation losses and visceral/skeletal abnormalities were seen at higher exposures, which are considered secondary to maternal hypoglycemia. These effects were similar to those observed in rats administered regular human insulin [see Data].

The estimated background risk of major birth defects is 6-10% in women with pre-gestational diabetes with a HbA1c>7% and has been reported to be as high as 20-25% in women with a HbA1c>10%. The estimated background risk of miscarriage for the indicated population is unknown. In the U.S. general population, the estimated background risk of major birth defects and miscarriage in clinically recognized pregnancies is 2-4% and 15-20%, respectively.

Clinical Considerations

Disease-Associated Maternal and/or Embryo-Fetal Risk

Poorly controlled diabetes in pregnancy increases the maternal risk for diabetic ketoacidosis, preeclampsia, spontaneous abortions, preterm delivery, and delivery complications. Poorly controlled diabetes increases the fetal risk for major birth defects, still birth, and macrosomia related morbidity.

Data

Human Data

Published data from 5 randomized controlled trials of 441 pregnant women with diabetes mellitus treated with insulin aspart during the late 2ndtrimester of pregnancy did not identify an association of insulin aspart with major birth defects or adverse maternal or fetal outcomes. However, these studies cannot definitely establish the absence of any risk because of methodological limitations, including a variable duration of treatment and small size of the majority of the trials.

Animal Data

Fertility, embryo-fetal and pre- and postnatal development studies have been performed with insulin aspart and regular human insulin in rats and rabbits. In a combined fertility and embryo-fetal development study in rats, insulin aspart was administered before mating, during mating, and throughout pregnancy. Further, in a pre- and postnatal development study insulin aspart was given throughout pregnancy and during lactation to rats. In an embryo-fetal development study insulin aspart was given to female rabbits during organogenesis. The effects of insulin aspart did not differ from those observed with subcutaneous regular human insulin. Insulin aspart, like human insulin, caused pre- and post-implantation losses and visceral/skeletal abnormalities in rats at a dose of 200 units/kg/day (approximately 32 times the human subcutaneous dose of 1 unit/kg/day, based on human exposure equivalents) and in rabbits at a dose of 10 units/kg/day (approximately three times the human subcutaneous dose of 1 unit/kg/day, based on human exposure equivalents). No significant effects were observed in rats at a dose of 50 units/kg/day and in rabbits at a dose of 3 units/kg/day. These doses are approximately 8 times the human subcutaneous dose of 1 unit/kg/day for rats and equal to the human subcutaneous dose of 1 unit/kg/day for rabbits, based on human exposure equivalents. The effects are considered secondary to maternal hypoglycemia.

8.2 Lactation

Risk Summary

There are no data on the presence of NOVOLOG MIX 70/30 in human milk, the effects on the breastfed infant, or the effect on milk production. One small published study reported that exogenous insulin, including insulin aspart, was present in human milk. However, there is insufficient information to determine the effects of insulin aspart on the breastfed infant. The developmental and health benefits of breastfeeding should be considered along with the mother’s clinical need for NOVOLOG MIX 70/30, and any potential adverse effects on the breastfed infant from NOVOLOG MIX 70/30, or from the underlying maternal condition.

8.4 Pediatric Use

Safety and effectiveness of NOVOLOG MIX 70/30 have not been established in pediatric patients with diabetes mellitus.

8.5 Geriatric Use

Clinical studies of NOVOLOG MIX 70/30 did not include sufficient numbers of patients aged 65 and over to determine whether they respond differently than younger adult patients. In geriatric patients with diabetes, the initial dosing, dose increments should be conservative to avoid hypoglycemic reactions. Hypoglycemia may be difficult to recognize in geriatric patients.

8.6 Renal Impairment

The effect of renal impairment on the pharmacokinetics of NOVOLOG MIX 70/30 has not been studied. Some studies with human insulin have shown increased circulating levels of insulin in patients with renal failure. Patients with renal impairment may be at increased risk of hypoglycemia and may require more frequent NOVOLOG MIX 70/30 dose adjustment and more frequent blood glucose monitoring [see Warnings and Precautions (5.3)].

8.7 Hepatic Impairment

The effect of hepatic impairment on the pharmacokinetics of NOVOLOG MIX 70/30 has not been studied. Patients with hepatic impairment may be at increased risk of hypoglycemia and may require more frequent NOVOLOG MIX 70/30 dose adjustment and more frequent blood glucose monitoring [see Warnings and Precautions (5.3)].

10 OVERDOSAGE

Excess insulin administration may cause hypoglycemia and hypokalemia [see Warnings and Precautions (5.3, 5.6)].Mild episodes of hypoglycemia usually can be treated with oral glucose. Adjustments in drug dosage, meal patterns, or exercise, may be needed. More severe episodes with coma, seizure, or neurologic impairment may be treated with intramuscular/subcutaneous glucagon or concentrated intravenous glucose. Sustained carbohydrate intake and observation may be necessary because hypoglycemia may recur after apparent clinical recovery. Hypokalemia must be corrected appropriately.

11 DESCRIPTION

Insulin aspart protamine and insulin aspart is a human insulin analog containing 70% insulin aspart protamine crystals and 30% soluble insulin aspart. Insulin aspart is homologous with regular human insulin with the exception of a single substitution of the amino acid proline by aspartic acid in position B28, and is produced by recombinant DNA technology utilizing Saccharomyces cerevisiae(baker’s yeast). Insulin aspart has the empirical formula C256H381N65O79S6and a molecular weight of 5825.8 Da.

Figure 1. Structural formula of insulin aspart

NOVOLOG MIX 70/30 (insulin aspart protamine and insulin aspart) is a uniform, white and cloudy, sterile injectable suspension for subcutaneous use. Each mL contains 100 units of insulin aspart and the inactive ingredients: disodium hydrogen phosphate dihydrate (1.25 mg), glycerol (16.0 mg), metacresol (1.72 mg), phenol (1.50 mg), protamine sulfate (0.32 mg), sodium chloride (0.877 mg), zinc (19.6 mcg), and Water for Injection, USP. NOVOLOG MIX 70/30 has a pH of 7.20 - 7.44. Hydrochloric acid or sodium hydroxide may be added to adjust pH.

12 CLINICAL PHARMACOLOGY

12.1 Mechanism of Action

The primary activity of insulin, including NOVOLOG MIX 70/30 is the regulation of glucose metabolism. Insulin and its analog lower blood glucose by stimulating peripheral glucose uptake, especially by skeletal muscle and fat, and by inhibiting hepatic glucose production. Insulin inhibits lipolysis and proteolysis, and enhances protein synthesis.

12.2 Pharmacodynamics

A euglycemic clamp study described below assessed glucose utilization after subcutaneous dosing of NOVOLOG MIX 70/30 in healthy subjects (n = 24). Following a 0.3 units/kg single subcutaneous dose of NOVOLOG MIX 70/30, the onset of action is between 10-20 minutes and the mean ± SD time to peak activity is 2.7 hr ± 0.9 hr. The duration of action may be as long as 24 hours (see Figure 2).

Figure 2. Pharmacodynamic Activity Profile of NOVOLOG MIX 70/30 in healthy subjects after a single 0.3 units/kg subcutaneous dose

12.3 Pharmacokinetics

The single substitution of the amino acid proline with aspartic acid at position B28 in insulin aspart (NOVOLOG) reduces the molecule’s tendency to form hexamers as observed with regular human insulin. The rapid absorption characteristics of NOVOLOG are maintained by NOVOLOG MIX 70/30.

Absorption and Bioavailability

The 30% insulin aspart in the soluble component of NOVOLOG MIX 70/30 is absorbed rapidly from the subcutaneous layer. The remaining 70% is in crystalline form as insulin aspart protamine which has a prolonged absorption profile after subcutaneous injection.

The relative bioavailability of NOVOLOG MIX 70/30 compared to NOVOLOG indicates that the insulins are absorbed to similar extent. In a euglycemic clamp study in healthy subjects (n=24) after dosing with NOVOLOG MIX 70/30 (0.3 units/kg), a mean maximum serum concentration (Cmax) of 61.3 ± 20.1 milliunits/L was reached after 85 minutes. Serum insulin levels returned to baseline 16 to 20 hours after a subcutaneous dose of NOVOLOG MIX 70/30 (see Fig. 3 for pharmacokinetic profile).

Figure 3. Pharmacokinetic Profile of NOVOLOG MIX 70/30 after a single 0.3 units/kg subcutaneous dose

Distribution and Elimination

Insulin aspart has a low binding affinity to plasma proteins (<10%), similar to that seen with regular human insulin.

13 NONCLINICAL TOXICOLOGY

13.1 Carcinogenesis, Mutagenesis, Impairment of Fertility

Standard 2-year carcinogenicity studies in animals have not been performed to evaluate the carcinogenic potential of NOVOLOG MIX 70/30. In 52-week studies, Sprague-Dawley rats were dosed subcutaneously with NOVOLOG, the rapid-acting component of NOVOLOG MIX 70/30, at 10, 50, and 200 units/kg/day (approximately 2, 8, and 32 times the human subcutaneous dose of 1.0 unit/kg/day, based on units/body surface area, respectively). At a dose of 200 units/kg/day, NOVOLOG increased the incidence of mammary gland tumors in females when compared to untreated controls. The relevance of these findings to humans is not known.

NOVOLOG was not genotoxic in the following tests: Ames test, mouse lymphoma cell forward gene mutation test, human peripheral blood lymphocyte chromosome aberration test, in vivomicronucleus test in mice, and in ex vivo UDS test in rat liver hepatocytes.

In fertility studies in male and female rats, NOVOLOG at subcutaneous doses up to 200 units/kg/day (approximately 32 times the human subcutaneous dose, based on units/body surface area) had no direct adverse effects on male and female fertility, or on general reproductive performance of animals.

14 CLINICAL STUDIES

14.1 Clinical Studies in Adult Patients with Type 1 and Type 2 Diabetes

In a three-month, open-label trial, adult patients with type 1 (n=104) or type 2 (n=187) diabetes mellitus were treated twice daily (before breakfast and before supper) with NOVOLOG MIX 70/30 or Novolin 70/30. Patients had received insulin for at least 24 months before the study. Oral hypoglycemic agents were not allowed within 1 month prior to the study or during the study. The small changes in HbA1cwere comparable across the treatment groups (see Table 4).

For patients with type 1 diabetes mellitus (T1DM) the mean age was 43 years old, 64% were male, 100% were White, the mean body mass index (BMI) was 26.1 kg/m^2, and mean duration of diabetes mellitus was 15 years. For patients with type 2 diabetes mellitus (T2DM), the mean age was 63 years old, 54% were male, 100% were White, the BMI 28.1 kg/m^2, and the mean duration of diabetes mellitus was 15 years.

Table 4: Glycemic Parameters at the End of Treatment [Mean ± SD (n subjects)]

 | NOVOLOG MIX 70/30 | Novolin 70/30
Type 1, n=104
Fasting Blood Glucose (mg/dL) | 174 ± 64 (48) | 142 ± 59 (44)
1.5 Hour Post Breakfast (mg/dL) | 187 ± 82 (48) | 200 ± 82 (42)
1.5 Hour Post Dinner (mg/dL) | 162 ± 77 (47) | 171 ± 66 (41)
HbA1c(%) Baseline | 8.4 ± 1.2 (51) | 8.5 ± 1.1 (46)
HbA1c(%) Week 12 | 8.4 ± 1.1 (51) | 8.3 ± 1.0 (47)
Type 2, n=187
Fasting Blood Glucose (mg/dL) | 153 ± 40 (76) | 152 ± 69 (93)
1.5 Hour Post Breakfast (mg/dL) | 182 ± 65 (75) | 200 ± 80 (92)
1.5 Hour Post Dinner (mg/dL) | 168 ± 51 (75) | 191 ± 65 (93)
HbA1c(%) Baseline | 8.1 ± 1.2 (82) | 8.2 ± 1.3 (98)
HbA1c(%) Week 12 | 7.9 ± 1.0 (81) | 8.1 ± 1.1 (96)

The significance, with respect to the long-term clinical sequelae of diabetes, of the differences in postprandial hyperglycemia between treatment groups has not been established.

14.2 Clinical Studies in Adult Patients with Type 2 Diabetes with Insulin and Oral Antidiabetic Agents

Trial 1:

In a 34-week, open-label trial (Trial 1), insulin-naïve patients with type 2 diabetes mellitus currently treated with 2 oral antidiabetic agents were switched to treatment with metformin and pioglitazone. The mean age of the trial population was 53 years and mean duration of diabetes was 9.2 years. Forty-six percent were male. Eighty-five percent were White, 12% were Black and 3% were Asian. The mean BMI was approximately 32.4 kg/m^2. During an 8-week optimization period metformin and pioglitazone were increased to 2,500 mg per day and 30 or 45 mg per day, respectively. After the optimization period, patients were randomized to receive either NOVOLOG MIX 70/30 twice daily added on to the metformin and pioglitazone regimen or continue the current optimized metformin and pioglitazone therapy. NOVOLOG MIX 70/30 was started at a dose of 6 international units twice daily (before breakfast and before supper). Insulin doses were titrated to a pre-meal glucose goal of 80-110 mg/dL. The total daily insulin dose at the end of the study was 56.9 ± 30.5 international units.

Table 5: Combination Therapy with Metformin and Pioglitazone in Patients with Type 2 Diabetes Mellitus [Mean (SD)] (Trial 1)

Treatment duration 24-weeks | NOVOLOG MIX 70/30 + Metformin; + Pioglitazone | Metformin + Pioglitazone
HbA1c
Baseline mean ± SD (n) | 8.1 ± 1.0 (102) | 8.1 ± 1.0 (98)
End-of-study mean ± SD (n) - LOCF | 6.6 ± 1.0 (93) | 7.8 ± 1.2 (87)
Adjusted Mean change from baseline ± SE (n)* | -1.6 ± 0.1 (93) | -0.3 ± 0.1 (87)
Treatment difference mean ± SE* 95% CI* | -1.3 ± 0.1; (-1.6, -1.0)
Percentage of subjects reaching HbA1c<7.0% | 76% | 24%
Percentage of subjects reaching HbA1c≤6.5% | 59% | 12%
Fasting Blood Glucose (mg/dL)
Baseline Mean ± SD (n) | 173 ± 39.8 (93) | 163 ± 35.4 (88)
End of Study Mean ± SD (n) - LOCF | 130 ± 50.0 (90) | 162 ± 40.8 (84)
Adjusted Mean change from baseline ± SE (n)* | -43.0 ± 5.3 (90) | -3.9 ± 5.3 (84)
End-of-Study Blood Glucose (Plasma) (mg/dL)
2 Hour Post Breakfast | 138 ± 42.8 (86) | 188 ± 57.7 (74)
2 Hour Post Lunch | 150 ± 41.5 (86) | 176 ± 56.5 (74)
2 Hour Post Dinner | 141 ± 57.8 (86) | 195 ± 60.1 (74)

- *Adjusted mean per group, treatment difference, and 95% CI were obtained based on an ANCOVA model with treatment, FPG stratum, and secretagogue stratum as fixed factors and baseline HbA1cas the covariate.
- Trial 2:
- In a 28-week, open-label trial (Trial 2), insulin-naïve patients with type 2 diabetes with fasting plasma glucose above 140 mg/dL currently treated with metformin ± thiazolidinedione therapy were randomized to receive either NOVOLOG MIX 70/30 twice daily [before breakfast and before supper] or insulin glargine once daily (see Table 6). NOVOLOG MIX 70/30 was started at an average dose of 5-6 international units (0.07 ± 0.03 international units/kg) twice daily (before breakfast and before supper), and bedtime insulin glargine was started at 10-12 international units (0.13 ± 0.03 international units/kg). Insulin doses were titrated weekly by decrements or increments of -2 to +6 units per injection to a pre-meal glucose goal of 80-110 mg/dL. The metformin dose was adjusted to 2,550 mg/day. Approximately one-third of the patients in each group were also treated with pioglitazone (30 mg/day). Insulin secretagogues were discontinued in order to reduce the risk of hypoglycemia. Most patients were White (53%), and the mean initial weight was 90 kg.
- The mean age of the trial population was 53 years old and mean duration of diabetes was 9.5 years. Fifty three percent were male. Fifty-five percent were White, 15% Black, 27% were Hispanic, 2% were Asian and 2% were Other. The mean BMI was approximately 31.5 kg/m^2.

Table 6: Combination Therapy with Metformin ± Pioglitazone and Two Types of Insulin in Patients with Type 2 Diabetes Mellitus [Mean (SD)] (Trial 2)

Treatment duration 28-weeks | NOVOLOG MIX 70/30 + Metformin ± Pioglitazone | Insulin Glargine + Metformin ± Pioglitazone
Number of patients | 117 | 116
HbA1c
Baseline mean (%) | 9.7 ± 1.5 (117) | 9.8 ± 1.4 (114)
End-of-study mean (± SD) | 6.9 ± 1.2 (108) | 7.4 ± 1.2 (114)
Mean change from baseline | -2.7 ± 1.6 (108) | -2.4 ± 1.5 (114)
Percentage of subjects reaching HbA1c<7.0% | 66% | 40%

16 HOW SUPPLIED/STORAGE AND HANDLING

NOVOLOG MIX 70/30 (insulin aspart protamine and insulin aspart) is a white and cloudy injectable suspension containing 100 units/mL (U-100) of 70% insulin aspart protamine and 30% insulin aspart available as:

The NOVOLOG MIX 70/30 FlexPen dials in 1-unit increments.

NDC: 70518-2119-00

PACKAGING: 5 in 1 CARTON, 3 mL in 1 SYRINGE PLASTIC TYPE 2

Dispense in the original sealed carton with the enclosed Instructions for Use. Store unused NOVOLOG MIX 70/30 in a refrigerator between 2°C to 8°C (36°F to 46°F). Do not freeze NOVOLOG MIX 70/30 or use NOVOLOG MIX 70/30 if it has been frozen. Do not expose NOVOLOG MIX 70/30 to excessive heat or light.

Always remove the needle after each injection and store NOVOLOG MIX 70/30 FlexPen without a needle attached.

Not in-use (unopened) Room Temperature (up to 30°C [86°F]): 14 days

Not in-use (unopened) Refrigerated (2°C to 8°C [36°F 46°F]): until expiration date

In-use (opened) Room Temperature (up to 30°C [86°F]): 14 days (Do not refrigerate)

Repackaged and Distributed By:

Remedy Repack, Inc.

625 Kolter Dr. Suite #4 Indiana, PA 1-724-465-8762

17 PATIENT COUNSELING INFORMATION

Advise the patient to read the FDA-approved patient labeling(Patient Information and Instructions for Use).

Never Share a NOVOLOG MIX 70/30 FlexPen between Patients

Advise patients that they must never share NOVOLOG MIX 70/30 FlexPen device with another person even if the needle is changed. Advise patients using NOVOLOG MIX 70/30 vials not to share needles or syringes with another person. Sharing poses a risk for transmission of blood-borne pathogens [see Warnings and Precautions (5.1)].

Hyperglycemia or Hypoglycemia

Inform patients that hypoglycemia is the most common adverse reaction with insulin. Instruct patients on self-management procedures including glucose monitoring, proper injection technique, and management of hypoglycemia and hyperglycemia, especially at initiation of NOVOLOG MIX 70/30 therapy. Instruct patients on handling of special situations such as intercurrent conditions (illness, stress, or emotional disturbances), an inadequate or skipped insulin dose, inadvertent administration of an increased insulin dose, inadequate food intake, and skipped meals. Instruct patients on the management of hypoglycemia [see Warnings and Precautions (5.3)].

Inform patients that their ability to concentrate and react may be impaired as a result of hypoglycemia. Advise patients who have frequent hypoglycemia or reduced or absent warning signs of hypoglycemia to use caution when driving or operating machinery.

Advise patients that changes in insulin regimen can predispose to hyperglycemia or hypoglycemia and that changes in insulin regimen should be made under close medical supervision [see Warnings and Precautions (5.2)] .

Hypoglycemia with Medication Errors

Instruct patients to always check the insulin label before each injection to avoid mix-ups between insulin products [see Warnings and Precautions (5.4)].

Hypersensitivity Reactions

Advise patients that hypersensitivity reactions have occurred with NOVOLOG MIX 70/30. Inform patients of the symptoms of hypersensitivity reactions [see Warnings and Precautions (5.5)].

Manufactured by:

Novo Nordisk Inc.

800 Scudders Mill Road

Plainsboro, NJ 08536

U.S. License Number 1261

Version: 18

Novo Nordisk®, NOVOLOG®, FlexPen®, and Novolin®are registered trademarks of Novo Nordisk®A/S.

ReliOn® is a registered trademark of Walmart Inc. and is used under license by Novo Nordisk Inc.

Patent Information: http://novonordisk-us.com/products/product-patents.html

© 2023 Novo Nordisk

For additional information about NOVOLOG MIX 70/30 contact:

www.novonordisk-us.com

Repackaged By / Distributed By: RemedyRepack Inc.

625 Kolter Drive, Indiana, PA 15701

(724) 465-8762

PATIENT INFORMATION

NovoLog®Mix 70/30 (NŌ-vō-log-MIX-SEV-en-tee-THIR-tee)

(insulin aspart protamine and insulin aspart)

injectable suspension, for subcutaneous use

Do not share your NovoLog Mix 70/30 FlexPen with other people, even if the needle has been changed. You may give other people a serious infection, or get a serious infection from them.

What is NovoLog Mix 70/30?

- NovoLog Mix 70/30 is a man-made insulin that is used to control high blood sugar in people with diabetes mellitus.
- It is not known if NovoLog Mix 70/30 is safe and effective in children.

Who should not take NovoLog Mix 70/30?

Do not take NovoLog Mix 70/30 if you:

- are having an episode of low blood sugar (hypoglycemia).
- have an allergy to NovoLog Mix 70/30 or any of the ingredients in NovoLog Mix 70/30.

Before taking NovoLog Mix 70/30, tell your healthcare provider about all your medical conditions including, if you are:

- pregnant, planning to become pregnant, or are breastfeeding.
- taking new prescription or over-the-counter medicines, vitamins, or herbal supplements.

Before you start taking NovoLog Mix 70/30, talk to your healthcare provider about low blood sugar and how to manage it.

How should I take NovoLog Mix 70/30?

- Read the Instructions for Usethat come with your NovoLog Mix 70/30.
- Take NovoLog Mix 70/30 exactly as your healthcare provider tells you to.
- NovoLog Mix 70/30 starts acting fast. If you have Type 1 diabetes, inject it up to 15 minutes before you eat a meal.Do not inject NovoLog Mix 70/30 if you are not planning to eat within 15 minutes. If you have Type 2 diabetes, you may inject NovoLog Mix 70/30 up to 15 minutes before or after starting your meal.
- Do not mixNovoLog Mix 70/30 with other insulin products oruse in an insulin pump.
- Know the type and strength of insulin you take. Do notchange the type of insulin you take unless your healthcare provider tells you to. The amount of insulin and the best time for you to take your insulin may need to change if you take different types of insulin.
- Check your blood sugar levels.Ask your healthcare provider what your blood sugars should be and when you should check your blood sugar levels.
- Do not reuse or share your needles or syringes with other people.You may give other people a serious infection or get a serious infection from them.
- NovoLog Mix 70/30 is injected under the skin (subcutaneously) of your stomach area, buttocks, upper legs, or upper arms.
- Change (rotate) your injection sites within the same area you choose with each doseto reduce your risk of getting lipodystrophy (pits in skin or thickened skin) and localized cutaneous amyloidosis (skin with lumps) at the injection sites.
  - Do notuse the exact same spot for each injection.
  - Do notinject where skin has pits, is thickened, or has lumps.
  - Do notinject where the skin is tender, bruised, scaly or hard, or into scars or damaged skin.

What should I avoid while taking NovoLog Mix 70/30?

While taking NovoLog Mix 70/30 do not:

- Drive or operate heavy machinery, until you know how NovoLog Mix 70/30 affects you.
- Drink alcohol or use prescription or over-the-counter medicines that contain alcohol.

What are the possible side effects of NovoLog Mix 70/30?

NovoLog Mix 70/30 may cause serious side effects that can lead to death, including:

Low blood sugar (hypoglycemia).Signs and symptoms that may indicate low blood sugar include:

- dizziness or light-headedness

- blurred vision

- anxiety, irritability, or mood changes

- sweating

- slurred speech

- hunger

- confusion

- shakiness

- headache

- fast heart beat

Your insulin dose may need to change because of:

- change in level of physical activity or exercise

- increased stress

- change in diet

- weight gain or loss

- illness

Other common side effects of NovoLog Mix 70/30 may include:

- low potassium in your blood (hypokalemia), reactions at the injection site, itching, rash, serious allergic reactions (whole body reactions), skin thickening or pits at the injection site (lipodystrophy), weight gain, and swelling of your hands and feet.

Get emergency medical help if you have:

- trouble breathing, shortness of breath, fast heartbeat, swelling of your face, tongue, or throat, sweating, extreme drowsiness, dizziness, confusion.

These are not all the possible side effects of NovoLog Mix 70/30. Call your doctor for medical advice about side effects. You may report side effects to FDA at 1-800-FDA-1088.

General information about the safe and effective use of NovoLog Mix 70/30.

Medicines are sometimes prescribed for purposes other than those listed in a Patient Information leaflet. You can ask your pharmacist or healthcare provider for information about NovoLog Mix 70/30 that is written for health professionals. Do not use NovoLog Mix 70/30 for a condition for which it was not prescribed. Do not give NovoLog Mix 70/30 to other people, even if they have the same symptoms that you have. It may harm them.

What are the ingredients in NovoLog Mix 70/30?

Active Ingredient:70% insulin aspart protamine and 30% insulin aspart.

Inactive Ingredients: disodium hydrogen phosphate dihydrate, glycerol, metacresol, phenol, protamine sulfate, sodium chloride, zinc, and Water for Injection, USP. Hydrochloric acid or sodium hydroxide may be added to adjust pH.

Manufactured by:Novo Nordisk Inc., Plainsboro, NJ 08536 U.S. License Number 1261

For more information, go to www.novonordisk-us.com or call 1-800-727-6500.

This Patient Information has been approved by the U.S. Food and Drug Administration

Revised: 2/2023

INSTRUCTIONS FOR USE

NovoLog® Mix 70/30

(insulin aspart protamine and insulin aspart)

injectable suspension, for subcutaneous use

10 mL multiple-dose vial (100 Units/mL, U-100)

Read this Instructions for Use before you start taking NovoLog Mix 70/30 and each time you get a refill. There may be new information. This information does not take the place of talking to your healthcare provider about your medical condition or your treatment.

Supplies you will need to give your NovoLog Mix 70/30 injection:

- 10 mL NovoLog Mix 70/30 vial
- insulin syringe and needle
- alcohol swabs

Preparing your NovoLog Mix 70/30 dose:

- Wash your hands with soap and water.
- Before you start to prepare your injection, check the NovoLog Mix 70/30 label to make sure that you are taking the right type of insulin. This is especially important if you use more than 1 type of insulin.
- NovoLog Mix 70/30 should look white and cloudy after mixing. Do notuse NovoLog Mix 70/30 if it looks clear or contains any lumps or particles.
- NovoLog Mix 70/30 is easier to mix when it is at room temperature.
- After mixing NovoLog Mix 70/30, inject your dose right away. If you wait to inject your dose, the insulin will need to be mixed again.
- Do notuse NovoLog Mix 70/30 past the expiration date printed on the label.

Step 1:If you are using a new vial, pull off the tamper-resistant cap (See Figure A).

Step 2:Wipe the rubber stopper with an alcohol swab (See Figure B).

Step 3:Roll the NovoLog Mix 70/30 vial between your hands 10 times. Keep the vial in a horizontal (flat) position (See Figure C). Roll the vial between your hands until the NovoLog Mix 70/30 looks white and cloudy. Do not shake the vial.

Step 4:Hold the syringe with the needle pointing up. Pull down on the plunger until the black tip reaches the line for the number of units for your prescribed dose (See Figure D).

Step 5:Push the needle through the rubber stopper of the NovoLog Mix 70/30 vial (See Figure E).

Step 6:Push the plunger all the way in. This puts air into the NovoLog Mix 70/30 vial (See Figure F).

Step 7:Turn the NovoLog Mix 70/30 vial and syringe upside down and slowly pull the plunger down until the black tip is a few units past the line for your dose (See Figure G).

- If there are air bubbles, tap the syringe gently a few times to let any air bubbles rise to the top (See Figure H).

Step 8:Slowly push the plunger up until the black tip reaches the line for your NovoLog Mix 70/30 dose (See Figure I).

Step 9:Check the syringe to make sure you have the right dose of NovoLog Mix 70/30.

Step 10:Pull the syringe out of the vial’s rubber stopper (See Figure J).

Giving your injection:

- Inject your NovoLog Mix 70/30 exactly as your healthcare provider has shown you. Your healthcare provider should tell you if you need to pinch the skin before injecting.
- NovoLog Mix 70/30 is injected under the skin (subcutaneously) of your stomach area, buttocks, upper legs, or upper arms.
- Change (rotate) your injection sites within the area you choose for each dose to reduce your risk of getting lipodystrophy (pits in skin or thickened skin) and localized cutaneous amyloidosis (skin with lumps) at the injection sites. Do notuse the same injection site for each injection. Do not inject where the skin has pits, thickened, or has lumps. Do not inject where the skin is tender, bruised, scaly or hard, or into scars or damaged skin.

Step 11:Choose your injection site and wipe the skin with an alcohol swab. Let the injection site dry before you inject your dose (See Figure K).

Step 12:Insert the needle into your skin. Push down on the plunger to inject your dose (See Figure L). The needle should remain in the skin for at least 6 seconds to make sure you have injected all the insulin.

Step 13:Pull the needle out of your skin. After that, you may see a drop of NovoLog Mix 70/30 at the needle tip. This is normal and does not affect the dose you just received (See Figure M).

- If you see blood after you take the needle out of your skin, press the injection site lightly with a piece of gauze or an alcohol swab. Do notrub the area.

After your injection:

- Do notrecap the needle. Recapping the needle can lead to a needle stick injury.
- Put the empty insulin vials, used needles and syringes in a FDA-cleared sharps disposal container right away after use. Do notthrow away (dispose of) loose needles and syringes in your household trash.
- If you do not have a FDA-cleared sharps disposal container, you may use a household container that is:
  - made of a heavy-duty plastic,
  - can be closed with a tight-fitting, puncture-resistant lid, without sharps being able to come out,
  - upright and stable during use,
  - leak-resistant, and
  - properly labeled to warn of hazardous waste inside the container.
- When your sharps disposal container is almost full, you will need to follow your community guidelines for the right way to dispose of your sharps disposal container. There may be state or local laws about how you should throw away used needles and syringes. For more information about the safe sharps disposal, and for specific information about sharps disposal in the state that you live in, go to the FDA’s website at: http://www.fda.gov/safesharpsdisposal.
  Do notdispose of your used sharps disposal container in your household trash unless your community guidelines permit this. Do notrecycle your used sharps disposal container.

How should I store NovoLog Mix 70/30?

- Do notfreeze NovoLog Mix 70/30. Do notuse NovoLog Mix 70/30 if it has been frozen.
- Keep NovoLog Mix 70/30 away from heat or light.
- All unopened vials:
- Store unopened NovoLog Mix 70/30 vials in the refrigerator at 36°F to 46°F (2°C to 8°C).
- Unopened vials may be used until the expiration date printed on the label, if they have been stored in the refrigerator.
- Unopened vials should be thrown away after 28 days, if they are stored at room temperature.
- After vials have been opened:
- Opened NovoLog Mix 70/30 vials can be stored in the refrigerator 36°F to 46°F (2°C to 8°C) or at room temperature below 86°F (30°C) for up to 28 days.
- Throw away all opened NovoLog Mix 70/30 vials after 28 days, even if they still have insulin left in them.

General information about the safe and effective use of NovoLog Mix 70/30

- Always use a new syringe and needle for each injection.
- Do not share syringes or needles.
- Keep NovoLog Mix 70/30 vials, syringes, and needles out of the reach of children.

This Instructions for Use has been approved by the U.S. Food and Drug Administration.

Manufactured by:

Novo Nordisk Inc.

800 Scudders Mill Road

Plainsboro, New Jersey 08536

1-800-727-6500

U.S. License Number 1261

Revised: 2/2023

NovoLog®is a registered trademark of Novo Nordisk A/S .

PATENT Information: http://novonordisk-us.com/products/product-patents.html

© 2023 Novo Nordisk

For information about NovoLog Mix 70/30 contact:

Novo Nordisk Inc.

800 Scudders Mill Road

Plainsboro, New Jersey 08536

1-800-727-6500

www.novonordisk-us.com

INSTRUCTIONS FOR USE

NovoLog®Mix 70/30 FlexPen®

(insulin aspart protamine and insulin aspart)

injectable suspension, for subcutaneous use

FlexPen®

Read the following instructions carefully before you start using your NovoLog Mix 70/30 FlexPen and each time you get a refill. There may be new information. You should read the instructions even if you have used NovoLog Mix 70/30 FlexPen before.

Do not share your NovoLog Mix 70/30 FlexPen with other people, even if the needle has been changed.You may give other people a serious infection, or get a serious infection from them.

NovoLog Mix 70/30 FlexPen is a disposable, single-patient-use dial-a-dose insulin pen. You can select doses from 1 to 60 units in increments of 1 unit. NovoLog Mix 70/30 FlexPen is designed to be used with NovoFine, NovoFine Plus or NovoTwist needles.

People who are blind or have vision problems should not use NovoLog Mix 70/30 FlexPen without help from a person trained to use NovoLog Mix 70/30 FlexPen.

Getting ready

Make sure you have the following items:

- NovoLog Mix 70/30 FlexPen
- New NovoFine, NovoFine Plus or NovoTwist needle
- Alcohol swabs

Preparing your NovoLog Mix 70/30 FlexPen

- Wash your hands with soap and water.
- Before you start to prepare your injection, check the label to make sure that you are taking the right type of insulin. This is especially important if you take more than 1 type of insulin. NovoLog Mix 70/30 should look cloudy after mixing.

Before your first injection with a new NovoLog Mix 70/30 FlexPen you must mix the insulin:

A. Let the insulin reach room temperature before you use it. This makes it easier to mix.

Pull off the pen cap (see diagram A).

B. Roll the pen between your palms 10 times - it is important that the pen is kept horizontal (see diagram B).

C. Then gently move the pen up and down ten times between position 1and 2as shown, so the glass ball moves from one end of the cartridge to the other (see diagram C).

Repeat rolling and moving the pen until the liquid appears white and cloudy. Do not use the pen if the liquid appears discolored or contains particles.

For every following injectionmove the pen up and down between positions 1 and 2 at least ten times until the liquid appears white and cloudy.

After mixing, complete all the following steps of the injection right away. If there is a delay, the insulin will need to be mixed again.

Wipe the rubber stopper with an alcohol swab.

Before you inject, there must be at least 12 units of insulin left in the cartridge to make sure the remaining insulin is evenly mixed. If there are less than 12 units left, use a new NovoLog Mix 70/30 FlexPen.

Attaching the needle

D. Remove the protective tab from a disposable needle.

Screw the needle tightly onto your NovoLog Mix 70/30 FlexPen. It is important that the needle is put on straight (see diagram D).

Never place a disposable needle on your NovoLog Mix 70/30 FlexPen until you are ready to take your injection.

E. Pull off the big outer needle cap (see diagram E).

F. Pull off the inner needle cap and throw it away (dispose of it) (see diagram F).

- Always use a new needle for each injection to make sure the needle is free of germs (sterile) and to prevent blocked needles. Do not reuse or share your needles or syringes with other people. You may give other people a serious infection, or get a serious infection from them.

Be careful not to bend or damage the needle before use.

To reduce the risk of a needle stick, never put the inner needle cap back on the needle.

Giving the airshot before each injection

Before each injection small amounts of air may collect in the cartridge during normal use. To avoid injecting air and to make sure you take the right dose of insulin:

G. Turn the dose selector to select 2 units (see diagram G).

H. Hold your NovoLog Mix 70/30 FlexPen with the needle pointing up. Tap the cartridge gently with your finger a few times to make any air bubbles collect at the top of the cartridge (see diagram H).

I. Keep the needle pointing upwards, press the push-button all the way in (see diagram I). The dose selector returns to 0.

A drop of insulin should appear at the needle tip. If not, change the needle and repeat the procedure no more than 6 times.

If you do not see a drop of insulin after 6 times, do not use the NovoLog Mix 70/30 FlexPen and contact Novo Nordisk at 1-800-727-6500.

A small air bubble may remain at the needle tip, but it will not be injected.

Selecting your dose

Check and make sure that the dose selector is set at 0.

J. Turn the dose selector to the number of units you need to inject. The pointer should line up with your dose.

The dose can be corrected either up or down by turning the dose selector in either direction until the correct dose lines up with the pointer (see diagram J). When turning the dose selector, be careful not to press the push-button as insulin will come out.

You cannot select a dose larger than the number of units left in the cartridge.

You will hear a click for every single unit dialed. Do not set the dose by counting the number of clicks you hear because you may get an incorrect dose.

Do not use the cartridge scale printed on the cartridge to measure your dose of insulin.

Giving the injection

- Do the injection exactly as shown to you by your healthcare provider. Your healthcare provider should tell you if you need to pinch the skin before injecting. Wipe the skin with an alcohol swab and let the area dry.
- NovoLog Mix 70/30 can be injected under the skin (subcutaneously) of your stomach area, buttocks, upper legs (thighs), or upper arms.
- Change (rotate) your injection sites within the area you choose for each dose to reduce your risk of getting lipodystrophy (pits in skin or thickened skin) and localized cutaneous amyloidosis (skin with lumps) at the injection sites. Do notuse the same injection site for each injection. Do not inject where the skin has pits, is thickened, or has lumps. Do not inject where the skin is tender, bruised, scaly or hard, or into scars or damaged skin.

K. Insert the needle into your skin.

Inject the dose by pressing the push-button all the way in until the 0 lines up with the pointer (see diagram K). Be careful only to push the button when injecting.

Turning the dose selector will not inject insulin.

L. Keep the needle in the skin for at least 6 seconds, and keep the push-button pressed all the way in until the needle has been pulled out from the skin (see diagram L). This will make sure that the full dose has been given.

You may see a drop of insulin at the needle tip. This is normal and has no effect on the dose you just received. If blood appears after you take the needle out of your skin, press the injection site lightly with an alcohol swab. Do not rub the area.

After the injection

Do not recap the needle.Recapping can lead to a needle stick injury. Remove the needle from the NovoLog Mix 70/30 FlexPen after each injection and dispose of it. This helps to prevent infection, leakage of insulin, and will help to make sure you inject the right dose of insulin.

- Put your used needles in a FDA-cleared sharps disposal container right away after use. Do not throw away (dispose of) loose needles in your household trash.
- If you do not have a FDA-cleared sharps disposal container, carefully slip the needle into the outer needle cap and throw it away in a household container that is:
  - made of a heavy-duty plastic,
  - can be closed with a tight-fitting, puncture-resistant lid, without sharps being able to come out,
  - upright and stable during use,
  - leak-resistant, and
  - properly labeled to warn of hazardous waste inside the container
- When your sharps disposal container is almost full, you will need to follow your community guidelines for the right way to dispose of your sharps disposal container. There may be state or local laws about how you should throw away used needles and syringes. For more information about the safe sharps disposal, and for specific information about sharps disposal in the state that you live in, go to the FDA’s website at: http://www.fda.gov/safesharpsdisposal.
- Do not dispose of your used sharps disposal container in your household trash unless your community guidelines permit this. Do not recycle your used sharps disposal container.
- When there is not enough medicine left in your NovoLog Mix 70/30 FlexPen for your prescribed dose, the NovoLog Mix 70/30 FlexPen may be thrown away in your household trash after you have removed the needle. The NovoLog Mix 70/30 FlexPen prevents the cartridge from being completely emptied. It is designed to deliver 300 units.

M. Put the pen cap on the NovoLog Mix 70/30 FlexPen and store the NovoLog Mix 70/30 FlexPen without the needle attached (see diagram M). Storing without the needle attached helps prevent leaking, blocking of the needle, and air from entering the Pen.

How should I store NovoLog Mix 70/30 FlexPen?

- Do notfreeze NovoLog Mix 70/30. Do notuse NovoLog Mix 70/30 if it has been frozen.
- Keep NovoLog Mix 70/30 away from heat or light.
- Store the NovoLog Mix 70/30 FlexPen without the needle attached.
- Unused NovoLog Mix 70/30 FlexPen:
  - Store unused NovoLog Mix 70/30 FlexPen in the refrigerator at 36°F to 46°F (2°C to 8°C).
  - Unused NovoLog Mix 70/30 FlexPen may be used until the expiration date printed on the label, if kept in the refrigerator.
  - Unused NovoLog Mix 70/30 FlexPen should be thrown away after 14 days, if it is stored at room temperature.
- In-Use NovoLog Mix 70/30 FlexPen:
  - Store the FlexPen you are currently using at room temperature below 86°F (30°C) for up to 14 days.
  - The NovoLog Mix 70/30 FlexPen you are using should be thrown away after 14 days, even if it still has insulin left in it.

Maintenance

For the safe and proper use of your NovoLog Mix 70/30 FlexPen be sure to handle it with care. Avoid dropping your NovoLog Mix 70/30 FlexPen as it may damage it. If you are concerned that your NovoLog Mix 70/30 FlexPen is damaged, use a new one. You can clean the outside of your NovoLog Mix 70/30 FlexPen by wiping it with a damp cloth. Do not soak or wash your NovoLog Mix 70/30 FlexPen as it may damage it. Do not refill your NovoLog Mix 70/30 FlexPen.

Remove the needle from the NovoLog Mix 70/30 FlexPen after each injection. This helps to ensure sterility, prevent leakage of insulin, and will help to make sure you inject the right dose of insulin for future injections.

Be careful when handling used needles to avoid needle sticks and transfer of infectious diseases.

Keep your NovoLog Mix 70/30 FlexPen and needles out of the reach of children.

Use NovoLog Mix 70/30 FlexPen as directed to treat your diabetes.

Do notshare your NovoLog Mix 70/30 FlexPen or needles with other people. You may give other people a serious infection, or get a serious infection from them.

Always use a new needle for each injection.

Novo Nordisk is not responsible for harm due to using this insulin pen with products not recommended by Novo Nordisk.

As a precautionary measure, always carry a spare insulin delivery device in case your NovoLog Mix 70/30 FlexPen is lost or damaged.

Remember to keep the disposable NovoLog Mix 70/30 FlexPen with you. Do not leave it in a car or other location where it can get too hot or too cold.

This Instructions for Use has been approved by the U.S. Food and Drug Administration.

Manufactured by:

Novo Nordisk Inc.

800 Scudders Mill Road

Plainsboro, New Jersey 08536

1-800-727-6500

U.S. License Number 1261

Revised: 2/2023

PACKAGE LABEL

DRUG: NovoLog Mix 70/30

GENERIC: insulin aspart

DOSAGE: INJECTION, SUSPENSION

ADMINSTRATION: SUBCUTANEOUS

NDC: 70518-2119-0

PACKAGING: 3 mL in 1 SYRINGE, PLASTIC

OUTER PACKAGING: 5 in 1 CARTON

ACTIVE INGREDIENT(S):

- INSULIN ASPART 100[iU] in 1mL

INACTIVE INGREDIENT(S):

- SODIUM PHOSPHATE, DIBASIC, DIHYDRATE
- GLYCERIN
- HYDROCHLORIC ACID
- METACRESOL
- PHENOL
- PROTAMINE SULFATE
- SODIUM CHLORIDE
- SODIUM HYDROXIDE
- ZINC